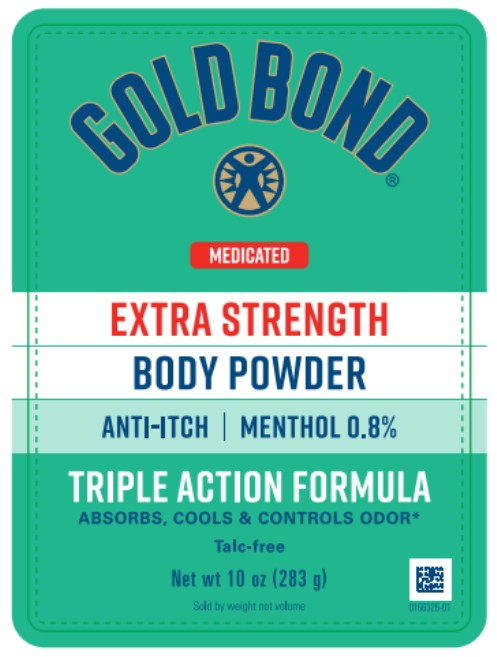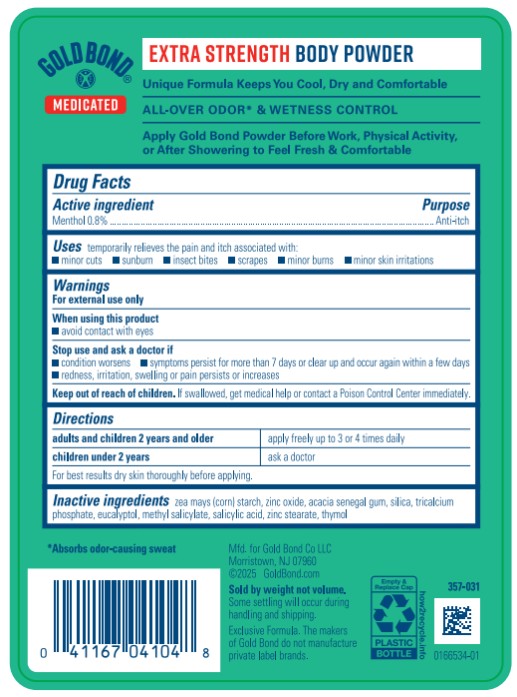 DRUG LABEL: Gold Bond Medicated Extra Strength Body
NDC: 84714-0410 | Form: POWDER
Manufacturer: Gold Bond Co LLC
Category: otc | Type: HUMAN OTC DRUG LABEL
Date: 20251204

ACTIVE INGREDIENTS: MENTHOL 0.8 g/100 g
INACTIVE INGREDIENTS: STARCH, CORN; ZINC OXIDE; ACACIA; SILICON DIOXIDE; TRICALCIUM PHOSPHATE; EUCALYPTOL; METHYL SALICYLATE; SALICYLIC ACID; ZINC STEARATE; THYMOL

Gold Bond Medicated Extra Strength Body Powder

Gold Bond Medicated

Extra Strength Body Powder

Drug Facts

Active ingredient

Menthol 0.8%

Purpose

Anti-itch

Uses

temporarily relieves the pain and itch associated with:

■ minor cuts ■ sunburn ■ insect bites ■ scrapes ■ minor burns ■ minor skin irritations

Warnings

For external use only

When using this product

■ avoid contact with eyes

Stop use and ask a doctor if

■ condition worsens

■ symptoms persist for more than 7 days or clear up and occur again within a few days

■ redness, irritation, swelling or pain persists or increases

Keep out of reach of children.

If swallowed, get medical help or contact a Poison Control Center immediately.

Directions

■ adults and children 2 years and older: apply freely up to 3 or 4 times daily

■ children under 2 years: ask a doctor

■ for best results dry skin thoroughly before applying

Inactive ingredients

zea mays (corn) starch, zinc oxide, acacia senegal gum, silica, tricalcium phosphate, eucalyptol, methyl salicylate, salicylic acid, zinc stearate, thymol

PRINCIPAL DISPLAY PANEL

GOLDBOND
EXTRA STRENGTH
BODY POWDER
Net wt 10 oz (283 g)